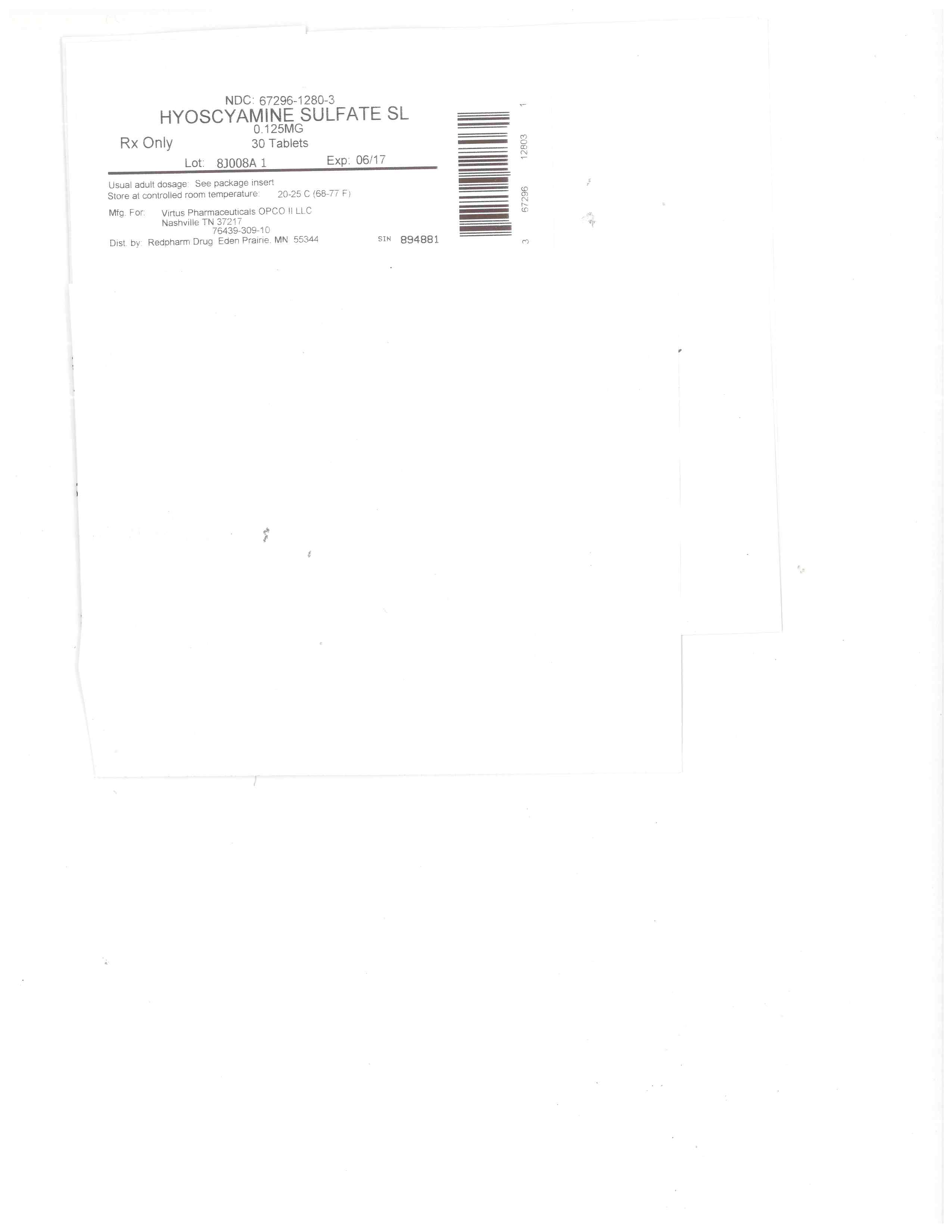 DRUG LABEL: Hyoscyamine Sulfate SL
NDC: 67296-1280 | Form: TABLET
Manufacturer: RedPharm Drug, Inc.
Category: prescription | Type: HUMAN PRESCRIPTION DRUG LABEL
Date: 20200120

ACTIVE INGREDIENTS: HYOSCYAMINE SULFATE 0.125 mg/1 1
INACTIVE INGREDIENTS: MANNITOL; CROSCARMELLOSE SODIUM; MAGNESIUM STEARATE

SPL UNCLASSIFIED SECTION

Rx Only.

DESCRIPTION

Hyoscyamine Sulfate Sublingual Tablets 0.125 mg are white, round, flat beveled edge tablets debossed "644" on one side. Plain on the other side.

Hyoscyamine Sulfate Sublingual tablets contain 0.125 mg hyoscyamine sulfate formulated for oral administration. Hyoscyamine sulfate is one of the principal anticholinergic/antispasmodic components of belladonna alkaloids. The molecular formula is (C17H23 NO3)2•H2SO4•2H2O and the molecular weight is 712.85. Chemically, it is benzeneacetic acid, α-(hydroxymethyl)-, 8-methyl-8-azabicyclo [3.2.1] oct-3-yl ester, [3(S)-endo]-, sulfate (2:1), dihydrate with the following structural formula:

[Chemical Structure]

Each tablet also contains as inactive ingredients: mannitol, croscarmellose sodium and magnesium stearate.

CLINICAL PHARMACOLOGY

Hyoscyamine sulfate inhibits specifically the actions of acetylcholine on structures innervated by postganglionic cholinergic nerves and on smooth muscles that respond to acetylcholine but lack cholinergic innervation. These peripheral cholinergic receptors are present in the autonomic effector cells of the smooth muscle, cardiac muscle, the sinoatrial node, the atrioventricular node, and the exocrine glands. At therapeutic doses, it is completely devoid of any action on autonomic ganglia. Hyoscyamine sulfate inhibits gastrointestinal propulsive motility and decreases gastric acid secretion. Hyoscyamine sulfate also controls excessive pharyngeal, tracheal and bronchial secretions. Hyoscyamine sulfate is absorbed totally and completely by sublingual administration as well as oral administration. Once absorbed, hyoscyamine sulfate disappears rapidly from the blood and is distributed throughout the entire body. The half-life of hyoscyamine sulfate is 2 to 3½ hours. Hyoscyamine sulfate is partly hydrolyzed to tropic acid and tropine but the majority of the drug is excreted in the urine unchanged within the first 12 hours. Only traces of this drug are found in breast milk. Hyoscyamine sulfate passes the blood brain barrier and the placental barrier.

INDICATIONS AND USAGE

Hyoscyamine sulfate is indicated whenever antispasmodic or anticholinergic therapy is desired. The high degree of purity allows effective action at very low dosage, with a minimal incidence of unwanted side effects.

CONTRAINDICATIONS

May be contraindicated in glaucoma, prostatic hypertrophy and some cases of cardiac disease.

SIDE EFFECTS

Excessive dryness of the mouth, blurred vision, urinary difficulty and tachycardia may indicate overdosage.

WARNINGS

In the presence of high environmental temperature, heat prostration can occur with drug use (fever and heat stroke due to decreased sweating). Diarrhea may be an early symptom of incomplete intestinal obstruction especially in patients with ileostomy or colostomy. In this instance, treatment with this drug would be inappropriate and possibly harmful. Like other anticholinergic agents, hyoscyamine sulfate may produce drowsiness, dizziness or blurred vision. In this event, the patient should be warned not to engage in activities requiring mental alertness such as operating a motor vehicle or other machinery or to perform hazardous work while taking this drug.

Psychosis has been reported in sensitive individuals given anticholinergic drugs including hyoscyamine sulfate. CNS signs and symptoms include confusion, disorientation, short term memory loss, hallucinations, dysarthria, ataxia, euphoria, anxiety, fatigue, insomnia, agitation and mannerisms, and inappropriate affect. These CNS signs and symptoms usually resolve within 12 to 48 hours after discontinuation of the drug.

PRECAUTIONS

General

Use with caution in patients with: autonomic neuropathy, hyperthyroidism, coronary heart disease, congestive heart failure, cardiac arrhythmias, hypertension, and renal disease. Investigate any tachycardia before giving any anticholinergic drug since they may increase the heart rate. Use with caution in patients with hiatal hernia associated with reflux esophagitis.

Information for Patients

Like other anticholinergic agents, hyoscyamine sulfate may produce drowsiness, dizziness, or blurred vision. In this event, the patient should be warned not to engage in activities requiring mental alertness such as operating a motor vehicle or other machinery or to perform hazardous work while taking this drug.

Use of hyoscyamine sulfate may decrease sweating resulting in heat prostration, fever or heat stroke; febrile patients or those who may be exposed to elevated environmental temperatures should use caution.

Drug Interactions

Additive adverse effects resulting from cholinergic blockade may occur when hyoscyamine sulfate is administered concomitantly with other antimuscarinics, amantadine, haloperidol, phenothiazines, monoamine oxidase (MAO) inhibitors, tricyclic antidepressants or some antihistamines.

Antacids may interfere with the absorption of hyoscyamine sulfate. Administer hyoscyamine sulfate before meals; antacids after meals.

Carcinogenesis, Mutagenesis, Impairment of Fertility

No long-term studies in animals have been performed to determine the carcinogenic, mutagenic or impairment of fertility potential of hyoscyamine sulfate.

Pregnancy

Category C

Animal reproduction studies have not been conducted with hyoscyamine sulfate. It is also not known whether hyoscyamine sulfate can cause fetal harm when administered to a pregnant woman or can affect reproduction capacity. Hyoscyamine sulfate should be given to a pregnant woman only if clearly needed.

Nursing Mothers

Hyoscyamine sulfate is excreted in human milk. Caution should be exercised when hyoscyamine sulfate is administered to a nursing woman.

Geriatric Use

Reported clinical experience has not identified differences in safety between patients aged 65 and over and younger patients. In general, dose selection for an elderly patient should be cautious, usually starting at the low end of the dosing range, reflecting the greater frequency of decreased hepatic, renal, or cardiac function, and of concomitant disease or other drug therapy.

This drug is known to be substantially excreted by the kidney, and the risk of toxic reactions to this drug may be greater in patients with impaired renal function. Because elderly patients are more likely to have decreased renal function, care should be taken in dose selection, and it may be useful to monitor renal function.

ADVERSE REACTIONS

All of the following adverse reactions have been reported with hyoscyamine sulfate. Adverse reactions may include dryness of the mouth; urinary hesitancy and retention; blurred vision; tachycardia; palpitations; mydriasis; increased ocular tension; loss of taste; headache; nervousness; drowsiness; weakness; fatigue; dizziness; insomnia; nausea; vomiting; impotence; constipation; bloated feeling; abdominal pain; diarrhea; allergic reactions or drug idiosyncrasies; urticaria and other dermal manifestations; ataxia; speech disturbance; some degree of mental confusion and/or excitement (especially in elderly persons); short-term memory loss; hallucinations; and decreased sweating.

To report suspected adverse reactions, contact Virtus Pharmaceuticals, OPCO II, LLC at 1-855-255-6076 or FDA at 1-800-FDA-1088 or www.fda.gov/medwatch.

OVERDOSAGE

The signs and symptoms of overdose are headache, nausea, vomiting, blurred vision, dilated pupils, hot dry skin, dizziness, dryness of the mouth, difficulty in swallowing, and CNS stimulation. Measures to be taken are immediate lavage of the stomach and injection of physostigmine 0.5 to 2 mg intravenously and repeated as necessary up to a total of 5 mg. Fever may be treated symptomatically (tepid water sponge baths, hypothermic blanket). Excitement to a degree of which demands attention may be managed with sodium thiopental 2% solution given slowly intravenously or chloral hydrate (100-200 mL of a 2% solution) by rectal infusion. In the event of progression of the curare-like effect to paralysis of the respiratory muscles, artificial respiration should be instituted and maintained until effective respiratory action returns.

In rats, the LD50 for hyoscyamine is 375 mg/kg. Hyoscyamine sulfate is dialyzable.

DOSAGE AND ADMINISTRATION

Dosage may be adjusted according to the conditions and severity of symptoms. Hyoscyamine Sulfate Sublingual Tablets, 0.125 mg must be placed under the tongue when it will dissolve in seconds, then swallow with saliva. Administering with liquid is not necessary.

Adults and pediatric patients 12 years of age and older

1 to 2 tablets every four hours or as needed. Do not exceed 12 tablets in 24 hours.

Pediatric patients 2 to under 12 years of age

½ to 1 tablet every four hours or as needed. Do not exceed 6 tablets in 24 hours.

HOW SUPPLIED

Bottles of 100
NDC 76439-0309-10

Store at controlled room temperature 20°-25°C (68°-77°F); excursions permitted to 15°-30°C (59°-86°F). [See USP Controlled Room Temperature].

Dispense in tight, light-resistant containers as defined in USP/NF with a child-resistant closure.

KEEP THIS AND ALL DRUGS OUT OF THE REACH OF CHILDREN.

Call your doctor about side effects. You may report side effects by calling (813)283-1344.

SPL UNCLASSIFIED SECTION

Manufactured for:
Virtus Pharmaceuticals OPCO II, LLC.
Nashville, TN 37217
1-855-255-6076

L26I-VIR
Rev. 10/15